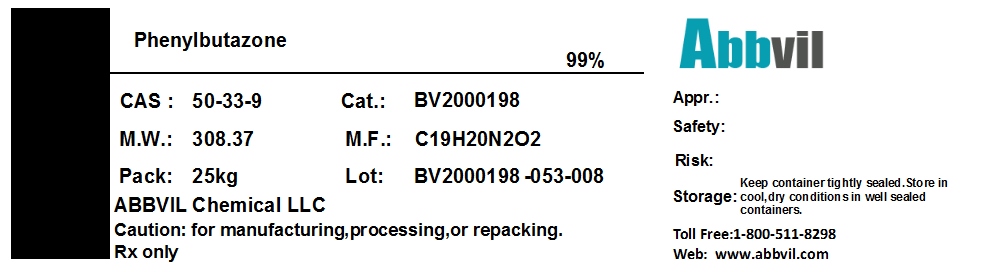 DRUG LABEL: PHENYLBUTAZONE
NDC: 86065-003 | Form: POWDER
Manufacturer: Abbvil Chemical LLC
Category: other | Type: BULK INGREDIENT
Date: 20160408

ACTIVE INGREDIENTS: PHENYLBUTAZONE 0.99 kg/1 kg

Phenylbutazone